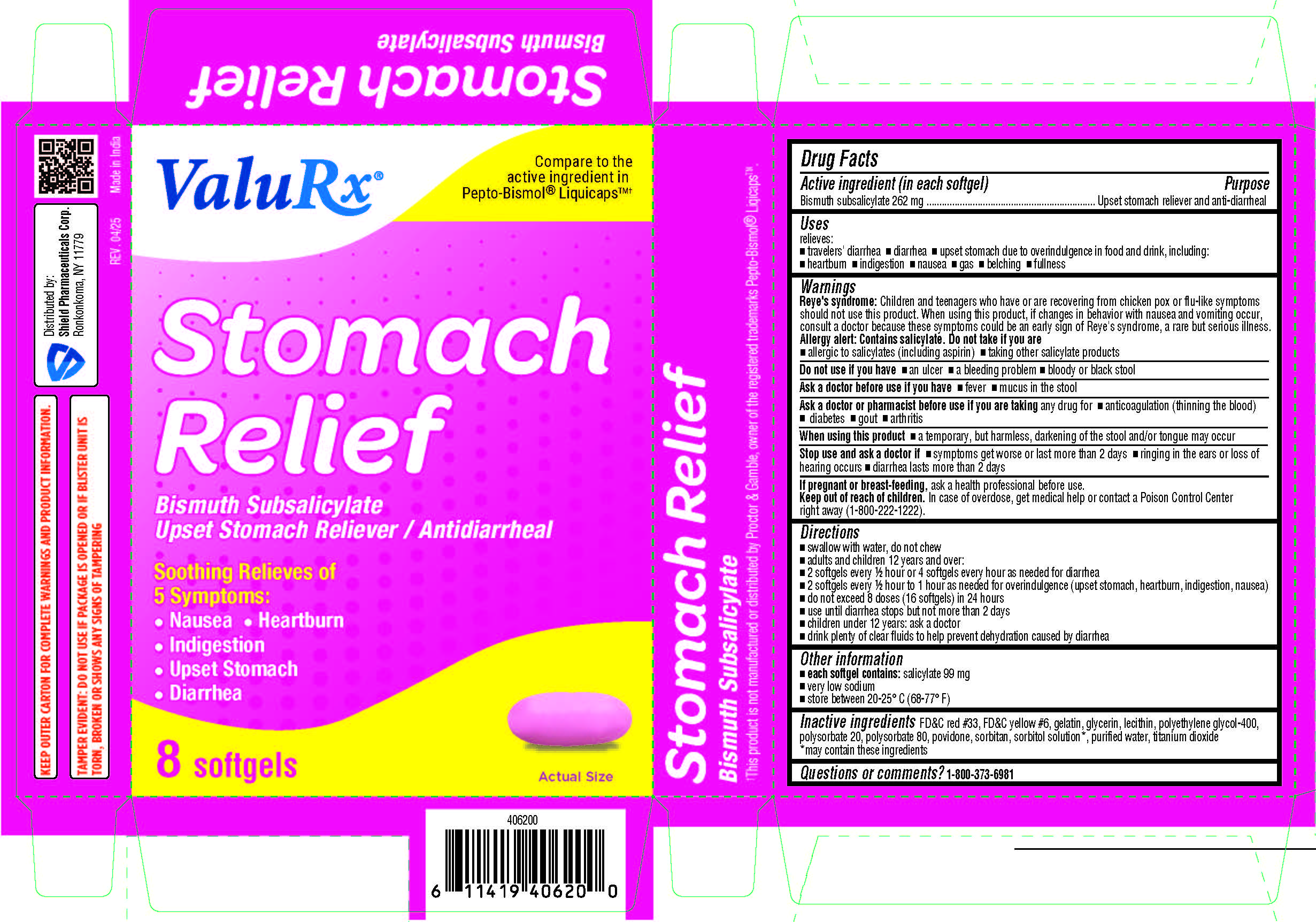 DRUG LABEL: Stomach Relief
NDC: 83059-0111 | Form: CAPSULE, LIQUID FILLED
Manufacturer: Shield Pharmaceuticals Corp
Category: otc | Type: HUMAN OTC DRUG LABEL
Date: 20251111

ACTIVE INGREDIENTS: BISMUTH 262 mg/1 1
INACTIVE INGREDIENTS: FD&C RED NO. 3; FD&C YELLOW NO. 6; GELATIN; GLYCERIN; LECITHIN, SOYBEAN; POLYETHYLENE GLYCOL 400; POLYSORBATE 20; POLYSORBATE 80; POVIDONE; SORBITOL; WATER; TITANIUM DIOXIDE

Stomach Relief

Drug Facts

Active ingredient (in each softgel)

Bismuth subsalicylate 262 mg

Purpose

Upset stomach reliever and anti-diarrheal

Uses

relieves:
• travelers' diarrhea
• diarrhea
• upset stomach due to
• overindulgence in food and drink, including:
• heartburn
• indigestion
• nausea
• gas
• belching
• fullness

Warnings

Reye's syndrome:Children and teenagers who have or are recovering from chicken pox or flu-like symptoms should not use this product. When using this product, if changes in behavior with nausea and vomiting occur, consult a doctor because these symptoms could be an early sign of Reye's syndrome, a rare but serious illness.
Allergy alert:Contains salicylate. Do not take if you are
• allergic to salicylates (including aspirin)
• taking other salicylate products

Do not use if you have
• an ulcer
• a bleeding problem
• bloody or black stool

Ask a doctor before use if you have
• fever
• mucus in the stool

Ask a doctor or pharmacist before use if you are taking any drug for

• any drug for
• anticoagulation (thinning the blood)
• diabetes
• gout
• arthritis

When using this product
• a temporary, but harmless, darkening of the stool and/or tongue may occur

Stop use and ask a doctor if
• symptoms get worse or last more than 2 days
• ringing in the ears or loss of hearing occurs
• diarrhea lasts more than 2 days

PREGNANCY OR BREAST FEEDING

If pregnant or breast-feeding,ask a health professional before use.

Keep out of reach of children.In case of overdose, get medical help or contact a Poison Control Center (1-800-222-1222) right away. Quick medical attention is critical for adults & for children even if you do not notice any signs or symptoms.

Directions

• swallow with water, do not chew
• adults and children 12 years and over:
• 2 softgels every ½ hour or 4 softgels every hour as needed for diarrhea
• 2 softgels every ½ hour to 1 hour as needed for overindulgence (upset stomach, heartburn, indigestion, nausea)
• do not exceed 8 doses (16 softgels) in 24 hours
• use until diarrhea stops but not more than 2 days
• children under 12 years: ask a doctor
• drink plenty of clear fluids to help prevent dehydration caused by diarrhea

Other information

• each softgel contains: salicylate 99 mg
• very low sodium
• store between 20-25° C (68-77° F)

Questions or comments?

1-800-373-6981 (toll-free)

Inactive ingredients

FD&C red #33, FD&C yellow #6, gelatin, glycerin, lecithin, polyethylene glycol-400, polysorbate 20, polysorbate 80, povidone, sorbitan, sorbitol solution*, purified water, titanium dioxide *may contain these ingredients

Distributed by:
Shield Pharmaceuticals Corp.
Ronkonkoma, NY 11779

PRINCIPAL DISPLAY PANEL

ValuRx

Compare to the active ingredient in Pepto-Bismol® LiquicapsTM†

Stomach Relief
Bismuth Subsalicylate
Upset Stomach Reliever/Antidiarrheal
Soothing Relieves of 5 Symptoms:
• Nausea
• Heartburn
• Indigestion
• Upset Stomach
• Diarrhea

Carton